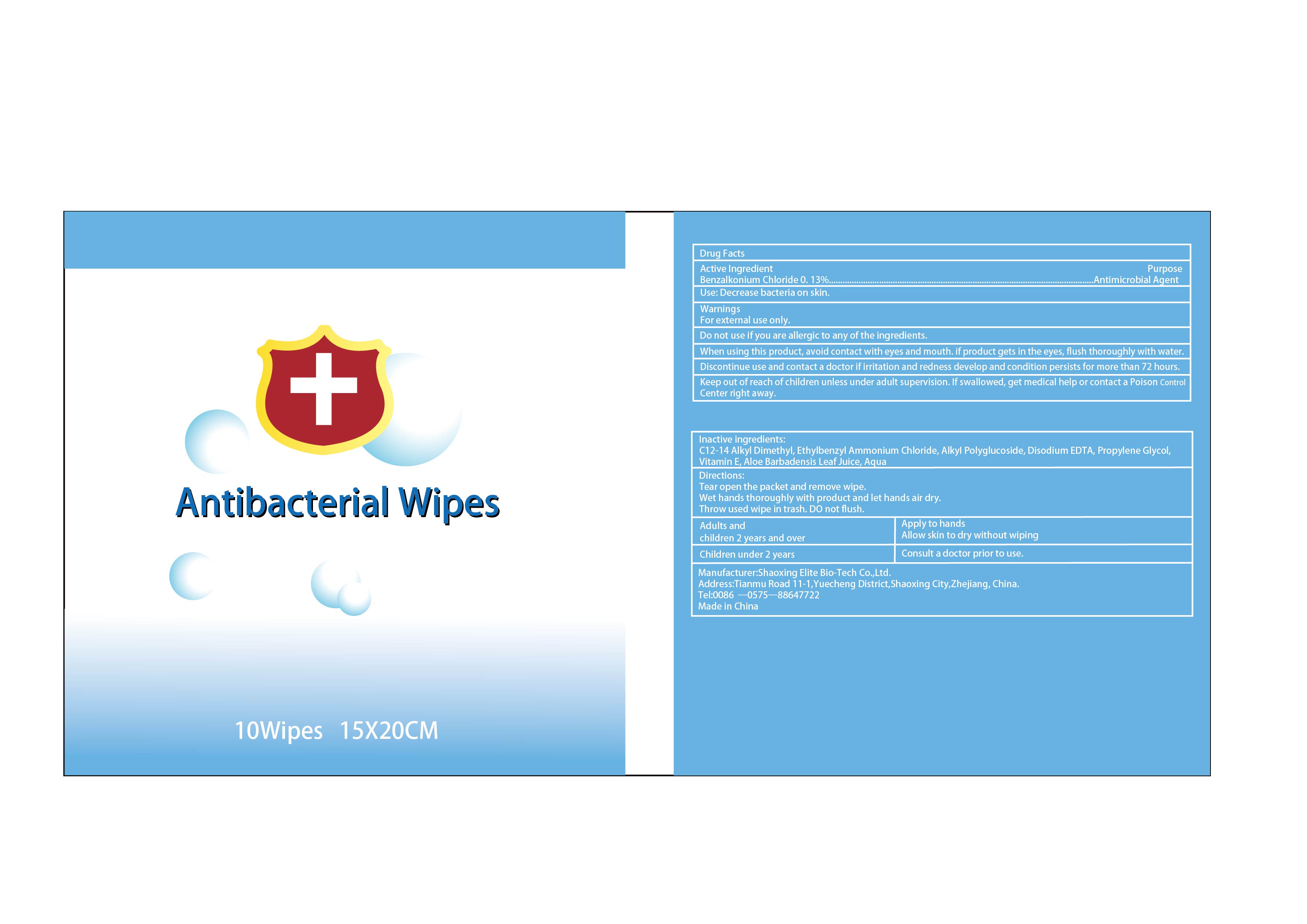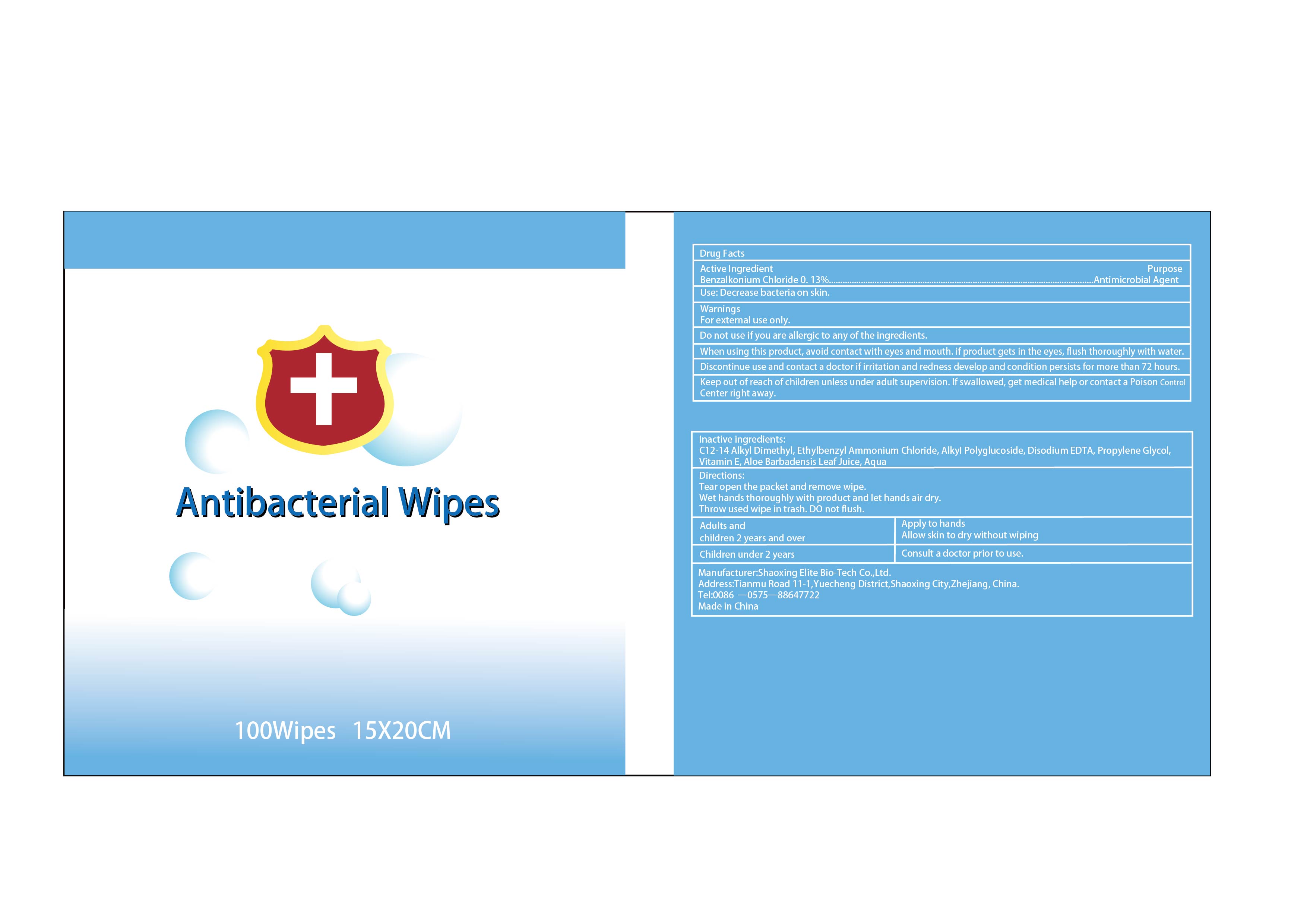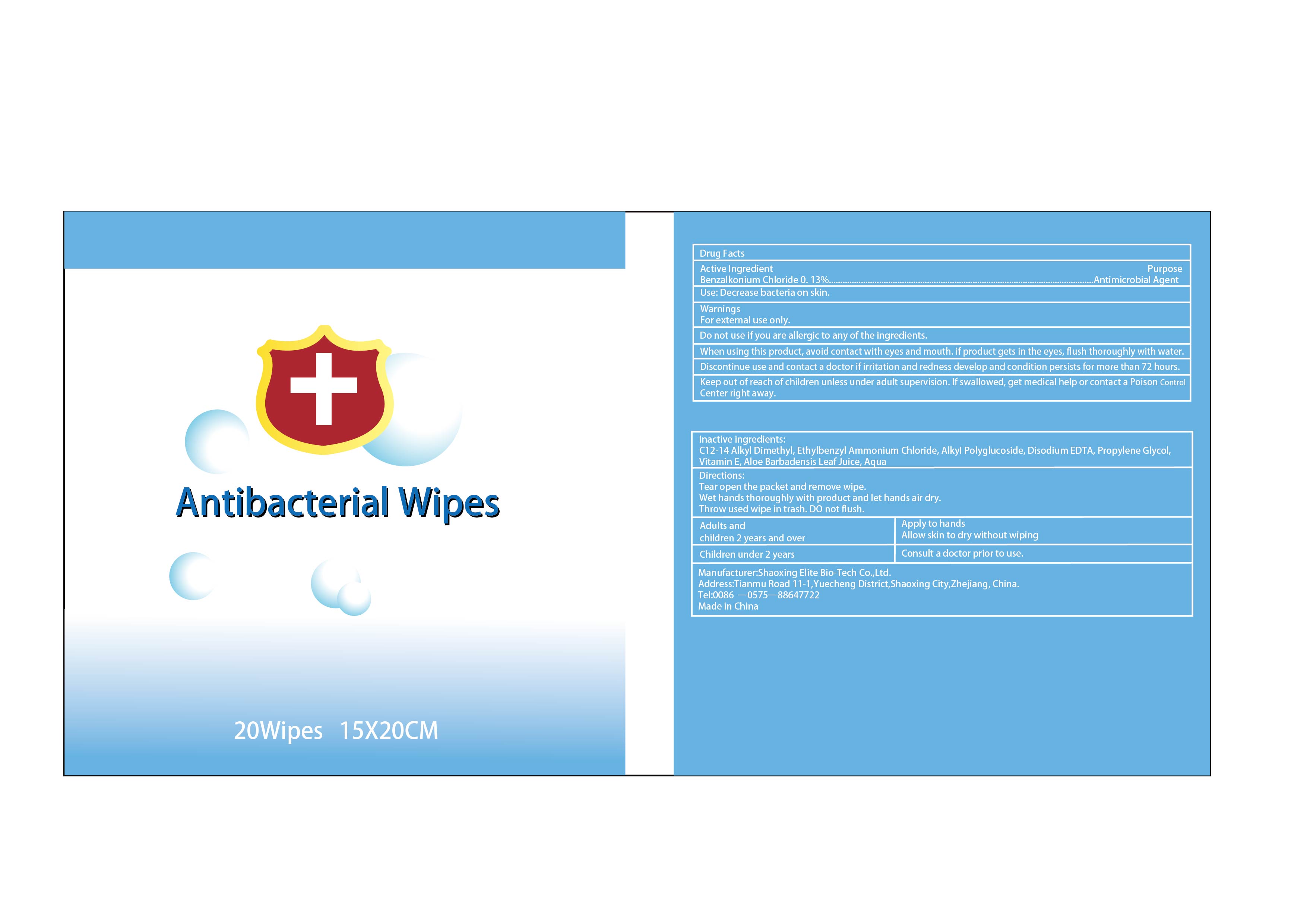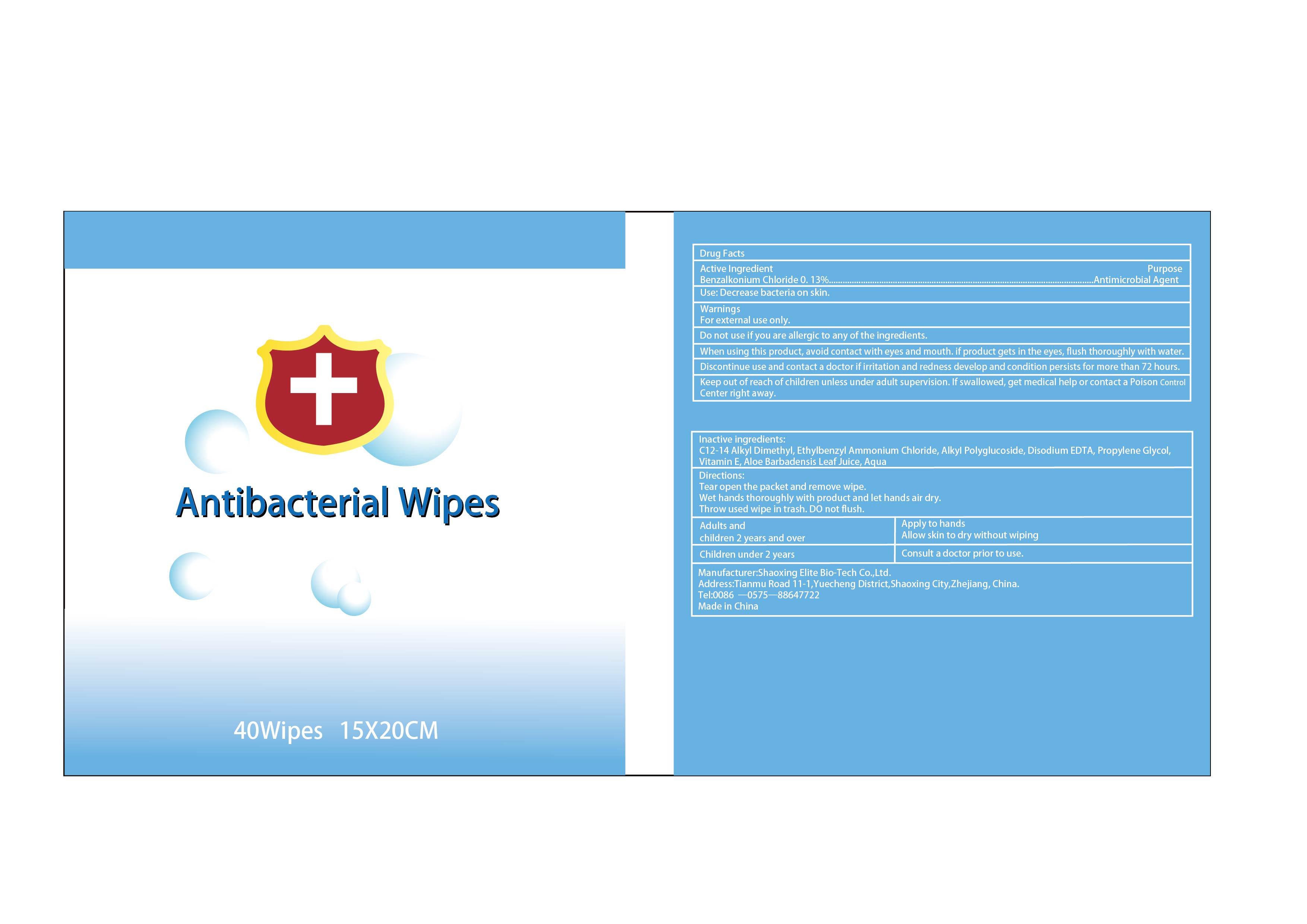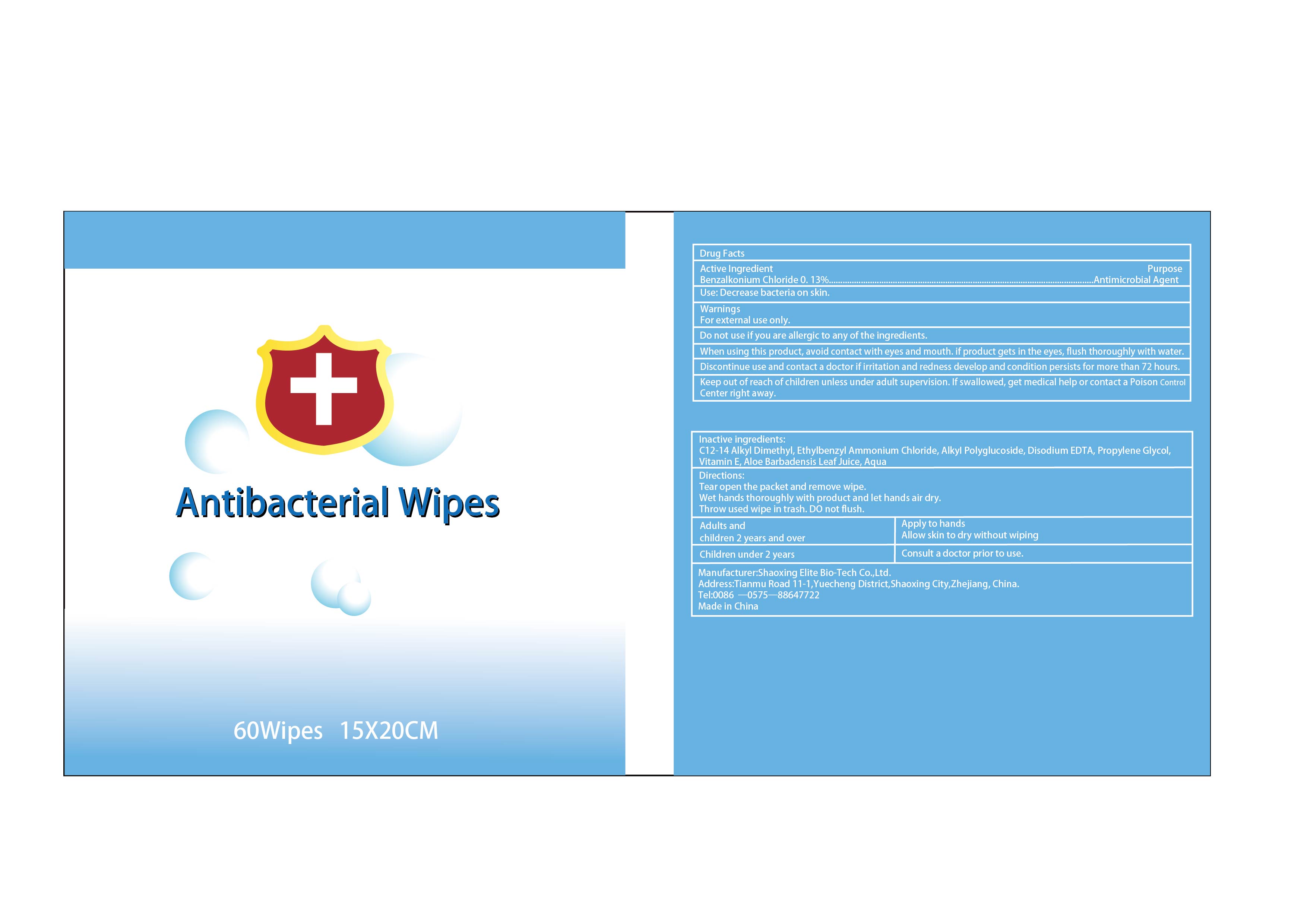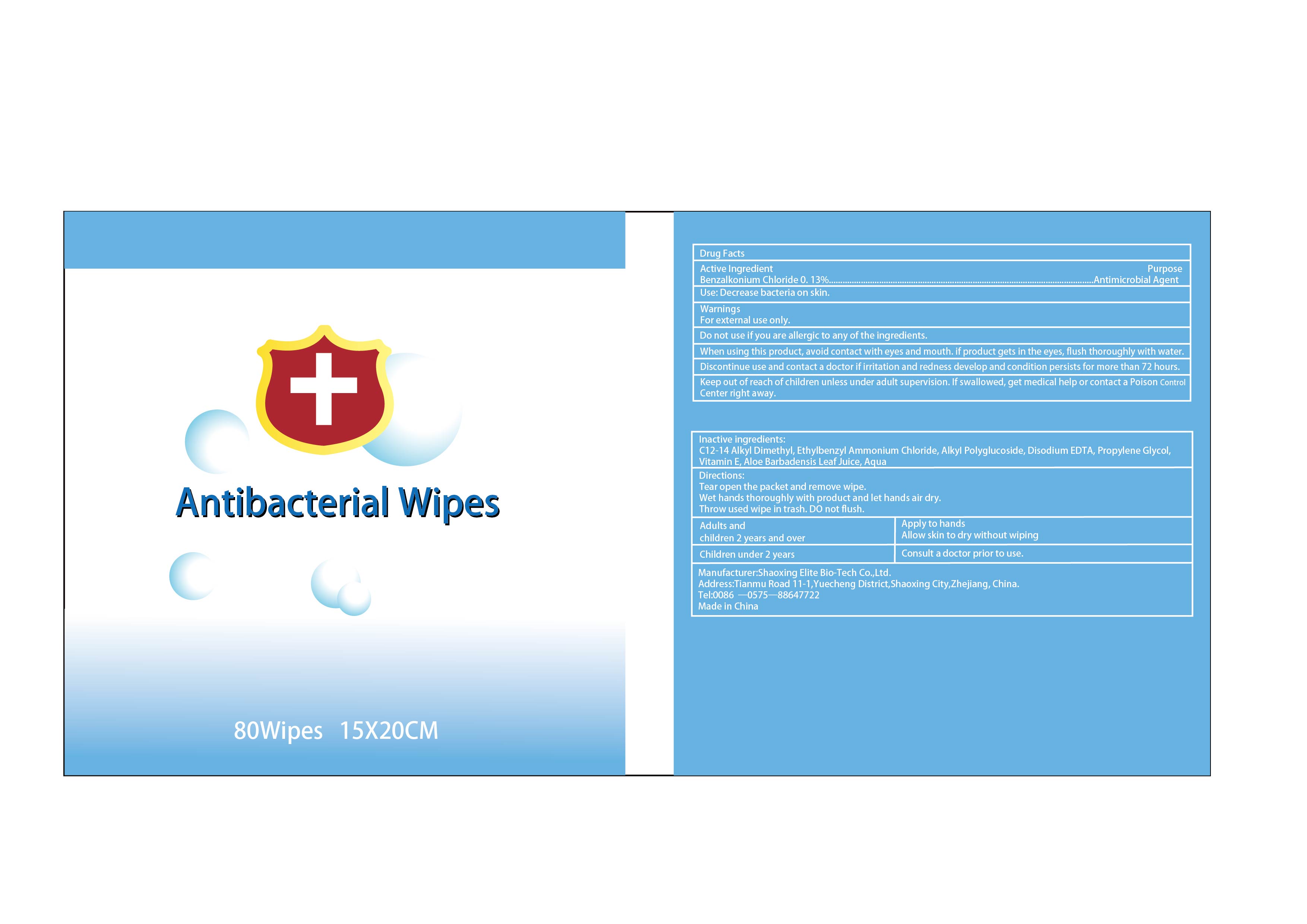 DRUG LABEL: Antibacterial Wipes
NDC: 81079-001 | Form: CLOTH
Manufacturer: SHAOXING ELITE BIO-TECH CO.,LTD.
Category: otc | Type: HUMAN OTC DRUG LABEL
Date: 20231122

ACTIVE INGREDIENTS: BENZALKONIUM CHLORIDE 0.13 g/100 g
INACTIVE INGREDIENTS: ALOE VERA LEAF; .ALPHA.-TOCOPHEROL; PROPYLENE GLYCOL; N-ALKYL ETHYLBENZYL DIMETHYL AMMONIUM CHLORIDE (C12-C14); DECYL GLUCOSIDE; WATER; EDETATE DISODIUM

Antibacterial Wipes

Drug Facts

Active Ingredient(s)

Benzalkonium Chloride 0.13%

Purpose

Antimicrobial Agent

Use

Decreases bacteria on skin.

Warnings

For external use only.

Do not use if you are allergic to any of the ingredients.

When using this product, avoid contact with eyes and mouth. lf product gets in the eyes, flush thoroughly with water.

STOP USE

Discontinue use and contact a doctor if irritation and redness develop and condition persists for more than 72 hours.

Keep out of reach of children unless under adult supervision. If swallowed, get medical help or contact a Poison Control Center right away.

Directions

Tear open the packet and remove wipe.

Wet hands thoroughly with product and let hands air dry.

Throw used wipe in trash.

Do not flush.

Other information

Adults and children 2 years and over. Apply to hands. Allow skin to dry without Wiping.

Children under 2 years. Consult a doctor prior to use.

Inactive ingredients

C12-14 Alkyl Dimethyl, Ethylbenzyl Ammonium Chloride, Alkyl Polyglucoside, Disodium EDTA, Propylene Glycol, Vitamin E, Aloe Barbadensis Leaf Juice, Aqua.

Antibacterial Wipes Package Label

NDC:81079-001-01

NDC:81079-001-02

NDC:81079-001-03

NDC:81079-001-04

NDC:81079-001-05

NDC:81079-001-06